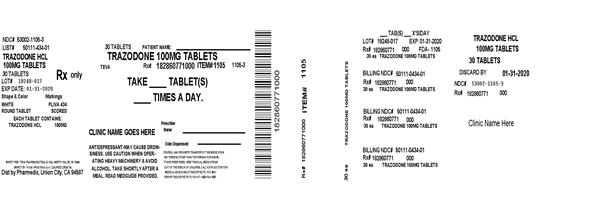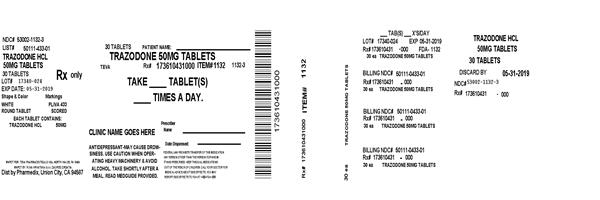 DRUG LABEL: Trazodone Hydrochloride
NDC: 53002-1105 | Form: TABLET
Manufacturer: RPK Pharmaceuticals, Inc.
Category: prescription | Type: HUMAN PRESCRIPTION DRUG LABEL
Date: 20230607

ACTIVE INGREDIENTS: TRAZODONE HYDROCHLORIDE 100 mg/1 1
INACTIVE INGREDIENTS: SILICON DIOXIDE; ANHYDROUS LACTOSE; MAGNESIUM STEARATE; MICROCRYSTALLINE CELLULOSE; SODIUM STARCH GLYCOLATE TYPE A POTATO

HIGHLIGHTS OF PRESCRIBING INFORMATION

These highlights do not include all the information needed to use TRAZODONE HYDROCHLORIDE TABLETS safely and effectively. See full prescribing information for TRAZODONE HYDROCHLORIDE TABLETS.
TRAZODONE HYDROCHLORIDE tablets, for oral use
Initial U.S. Approval: 1981

WARNING: SUICIDALITY AND ANTIDEPRESSANT DRUGS

See full prescribing information for complete boxed warning.

Increased risk of suicidal thinking and behavior in children, adolescents and young adults taking antidepressants for major depressive disorder (MDD) and other psychiatric disorders. Trazodone is not approved for use in pediatric patients (5.1).

1 INDICATIONS AND USAGE

Trazodone hydrochloride tablets are indicated for the treatment of major depressive disorder (1).

- Efficacy was established in trials of trazodone immediate release formulation in patients with major depressive disorder (14).

2 DOSAGE AND ADMINISTRATION

- Starting dose: 150 mg in divided doses daily. May be increased by 50 mg per day every three to four days. Maximum dose: 400 mg per day in divided doses (2).
- Trazodone hydrochloride tablets should be taken shortly after a meal or light snack (2).
- Tablets should be swallowed whole or broken in half along the score line, and should not be chewed or crushed (2).
- When discontinued, gradual dose reduction is recommended (2).

3 DOSAGE FORMS AND STRENGTHS

Bisectable tablets of 50 mg, 100 mg and 150 mg (3).

4 CONTRAINDICATIONS

None (4).

5 WARNINGS AND PRECAUTIONS

- Clinical Worsening/Suicide Risk: Monitor for clinical worsening and suicidal thinking and behavior (5.1).
- Serotonin Syndrome or Neuroleptic Malignant Syndrome-Like
  Reactions: Have been reported with antidepressants. Discontinue trazodone hydrochloride tablets and initiate supportive treatment (5.2, 7).
- Activation of Mania/Hypomania: Screen for bipolar disorder and monitor for mania/hypomania (5.3).
- QT Prolongation: Increases the QT interval. Avoid use with drugs that also increase the QT interval and in patients with risk factors for prolonged QT interval (5.4).
- Use in Patients With Heart Disease: Use with caution in patients with cardiac disease (5.5).
- Orthostatic Hypotension and Syncope: Have occurred. Warn patients of risk and symptoms of hypotension (5.6).
- Abnormal Bleeding: May increase the risk of bleeding. Use with NSAIDs, aspirin, or other drugs that affect coagulation may compound this risk (5.7, 7).
- Interaction With MAOIs: Do not use concomitantly or within 14 days of monoamine oxidase inhibitors (5.8, 7).
- Priapism: Has occurred. Warn male patients of this risk and how/when to seek medical attention (5.9).
- Hyponatremia: Can occur in association with SIADH (5.10).
- Potential for Cognitive and Motor Impairment: Has potential to impair judgment, thinking, and motor skills. Advise patients to use caution when operating machinery (5.11).
- Angle-Closure Glaucoma: Angle closure glaucoma has occurred in patients with untreated anatomically narrow angles treated with antidepressants. (5.12)
- Discontinuation Symptoms: May occur with abrupt discontinuation and include anxiety and sleep disturbance. Upon discontinuation, taper trazodone hydrochloride tablets and monitor for symptoms (5.13).

6 ADVERSE REACTIONS

Most common adverse reactions (incidence ≥ 5% and twice that of placebo) are: somnolence/sedation, dizziness, constipation, vision blurred (6).

To report SUSPECTED ADVERSE REACTIONS, contact TEVA USA, PHARMACOVIGILANCE at 1-866-832-8537 or drug.safety@tevapharm.com; or FDA at 1-800-FDA-1088 or www.fda.gov/medwatch

7 DRUG INTERACTIONS

- CNS Depressants: Trazodone may enhance effects of alcohol, barbiturates, or other CNS depressants (7).
- CYP3A4 Inhibitors: May necessitate lower dose of trazodone hydrochloride tablets (7).
- CYP3A4 Inducers (e.g., Carbamazepine): May necessitate higher dose of trazodone hydrochloride tablets (7).
- Digoxin or Phenytoin: Monitor for increased serum levels (7).
- Warfarin: Monitor for increased or decreased prothrombin time (7).

8 USE IN SPECIFIC POPULATIONS

- Pregnancy: Based on animal data, may cause fetal harm (8.1).
- Nursing Mothers: Use with caution (8.3).
- Pediatric Patients: Trazodone hydrochloride tablets are not approved in pediatric patients (8.4).
- Renal or Hepatic Impairment: Use with caution (8.6, 8.7).

FULL PRESCRIBING INFORMATION

WARNING: SUICIDALITY AND ANTIDEPRESSANT DRUGS

Antidepressants increased the risk compared to placebo of suicidal thinking and behavior (suicidality) in children, adolescents, and young adults in short-term studies of major depressive disorder (MDD) and other psychiatric disorders. Anyone considering the use of trazodone hydrochloride tablets or any other antidepressant in a child, adolescent, or young adult must balance this risk with the clinical need. Short-term studies did not show an increase in the risk of suicidality with antidepressants compared to placebo in adults beyond age 24; there was a reduction in risk with antidepressants compared to placebo in adults aged 65 and older. Depression and certain other psychiatric disorders are themselves associated with increases in the risk of suicide. Patients of all ages who are started on antidepressant therapy should be monitored appropriately and observed closely for clinical worsening, suicidality, or unusual changes in behavior. Families and caregivers should be advised of the need for close observation and communication with the prescriber. Trazodone hydrochloride tablets are not approved for use in pediatric patients [see Warnings and Precautions (5.1) and Patient Counseling Information (17.1)].

1 INDICATIONS AND USAGE

Trazodone hydrochloride tablets are indicated for the treatment of major depressive disorder (MDD) in adults. The efficacy of trazodone hydrochloride tablets has been established in trials with the immediate release formulation of trazodone [see Clinical Studies (14)].

2 DOSAGE AND ADMINISTRATION

The dosage should be initiated at a low-dose and increased gradually, noting the clinical response and any evidence of intolerance. Occurrence of drowsiness may require the administration of a major portion of the daily dose at bedtime or a reduction of dosage. Trazodone hydrochloride tablets should be taken shortly after a meal or light snack.

Dose Selection

An initial dose of 150 mg/day in divided doses is suggested. The dose may be increased by 50 mg/day every 3 to 4 days. The maximum dose for outpatients usually should not exceed 400 mg/day in divided doses. Inpatients (i.e., more severely depressed patients) may be given up to but not in excess of 600 mg/day in divided doses

- Once an adequate response has been achieved, dosage may be gradually reduced, with subsequent adjustment depending on therapeutic response.
- Patients should be monitored for withdrawal symptoms when discontinuing treatment with trazodone hydrochloride tablets. The dose should be gradually reduced whenever possible [see Warnings and Precautions (5.13)].

Maintenance Treatment

The efficacy of trazodone hydrochloride tablets for the maintenance treatment of MDD has not been evaluated. While there is no body of evidence available to answer the question of how long a patient treated with trazodone hydrochloride tablets should continue the drug, it is generally recommended that treatment be continued for several months after an initial response. Patients should be maintained on the lowest effective dose and be periodically reassessed to determine the continued need for maintenance treatment.

Important Administration Instructions

Trazodone hydrochloride tablets are scored to provide flexibility in dosing.

Trazodone hydrochloride tablets can be swallowed whole or administered as a half tablet by breaking the tablet along the score line.

3 DOSAGE FORMS AND STRENGTHS

Trazodone Hydrochloride Tablets USP are available in the following strengths:

50 mg: White, round, compressed tablet, debossed “PLIVA 433” on one side and scored on the other side.

100 mg: White, round, compressed tablet, debossed “PLIVA 434” on one side and scored on the other side.

150 mg: White, trapezoid, flat-faced, beveled edge tablet, scored and debossed as “PLIVA” bisect “441” on one side and tri-scored and debossed as “50” in each section on the other side.

4 CONTRAINDICATIONS

None.

5 WARNINGS AND PRECAUTIONS

5.1 Clinical Worsening and Suicide Risk

Patients with major depressive disorder (MDD), both adult and pediatric, may experience worsening of their depression and/or the emergence of suicidal ideation and behavior (suicidality) or unusual changes in behavior, whether or not they are taking antidepressant medications, and this risk may persist until significant remission occurs. Suicide is a known risk of depression and certain other psychiatric disorders and these disorders themselves are the strongest predictors of suicide. There has been a long standing concern, however, that antidepressants may have a role in inducing worsening of depression and the emergence of suicidality in certain patients during the early phases of treatment. Pooled analyses of short-term placebo-controlled trials of antidepressant drugs (SSRIs and others) showed that these drugs increase the risk of suicidal thinking and behavior (suicidality) in children, adolescents, and young adults (ages 18 to 24) with MDD and other psychiatric disorders. Short-term studies did not show an increase in the risk of suicidality with antidepressants compared to placebo in adults beyond age 24; there was a reduction with antidepressants compared to placebo in adults aged 65 and older.

The pooled analyses of placebo-controlled trials in children and adolescents with MDD, obsessive compulsive disorder (OCD), or other psychiatric disorders included a total of 24 short-term trials of 9 antidepressant drugs in over 4,400 patients. The pooled analyses of placebo-controlled trials in adults with MDD or other psychiatric disorders included a total of 295 short-term trials (median duration of 2 months) of 11 antidepressant drugs in over 77,000 patients. There was considerable variation in risk of suicidality among drugs, but a tendency toward an increase in the younger patients for almost all drugs studied. There were differences in absolute risk of suicidality across the different indications, with the highest incidence in MDD. The risk differences (drug vs. placebo), however, were relatively stable within age strata and across indications. These risk differences (drug-placebo difference in the number of cases of suicidality per 1,000 patients treated) are provided in Table 1.

Table 1
Age Range | Drug-Placebo Difference in Number of Cases; of Suicidality per 1,000 Patients Treated
 | Increases Compared to Placebo
< 18 | 14 additional cases
18 to 24 | 5 additional cases
 | Decreases Compared to Placebo
25 to 64 | 1 fewer case
≥ 65 | 6 fewer cases

No suicides occurred in any of the pediatric trials. There were suicides in the adult trials, but the number was not sufficient to reach any conclusion about drug effect on suicide.

It is unknown whether the suicidality risk extends to longer-term use, i.e., beyond several months. However, there is substantial evidence from placebo-controlled maintenance trials in adults with depression that the use of antidepressants can delay the recurrence of depression.

All patients being treated with antidepressants for any indication should be monitored appropriately and observed closely for clinical worsening, suicidality, and unusual changes in behavior, especially during the initial few months of a course of drug therapy, or at times of dose changes, either increases or decreases.

The following symptoms, anxiety, agitation, panic attacks, insomnia, irritability, hostility, aggressiveness, impulsivity, akathisia (psychomotor restlessness), hypomania, and mania, have been reported in adult and pediatric patients being treated with antidepressants for major depressive disorder as well as for other indications, both psychiatric and nonpsychiatric. Although a causal link between the emergence of such symptoms and either the worsening of depression and/or the emergence of suicidal impulses has not been established, there is concern that such symptoms may represent precursors to emerging suicidality.

Consideration should be given to changing the therapeutic regimen, including possibly discontinuing the medication, in patients whose depression is persistently worse, or who are experiencing emergent suicidality or symptoms that might be precursors to worsening depression or suicidality, especially if these symptoms are severe, abrupt in onset, or were not part of the patient's presenting symptoms.

Families and caregivers of patients being treated with antidepressants for major depressive disorder or other indications, both psychiatric and nonpsychiatric, should be alerted about the need to monitor patients for the emergence of agitation, irritability, unusual changes in behavior, and the other symptoms described above, as well as the emergence of suicidality, and to report such symptoms immediately to healthcare providers. Such monitoring should include daily observation by families and caregivers. Prescriptions for trazodone should be written for the smallest quantity of tablets consistent with good patient management, in order to reduce the risk of overdose.

5.2 Serotonin Syndrome or Neuroleptic Malignant Syndrome (NMS)-Like Reactions

The development of a potentially life-threatening serotonin syndrome or neuroleptic malignant syndrome (NMS)-like reactions have been reported with antidepressants alone and may occur with trazodone treatment, but particularly with concomitant use of other serotoninergic drugs (including SSRIs, SNRIs and triptans) and with drugs that impair metabolism of serotonin (including monoamine oxidase inhibitors [MAOIs]), or with antipsychotics or other dopamine antagonists. Serotonin syndrome symptoms may include mental status changes (e.g., agitation, hallucinations, and coma), autonomic instability (e.g., tachycardia, labile blood pressure, and hyperthermia), neuromuscular aberrations (e.g., hyperreflexia, incoordination) and/or gastrointestinal symptoms (e.g., nausea, vomiting, and diarrhea). Serotonin syndrome, in its most severe form, can resemble neuroleptic malignant syndrome, which includes hyperthermia, muscle rigidity, autonomic instability with possible rapid fluctuation of vital signs, and mental status changes.

Treatment with trazodone hydrochloride tablets and any concomitant serotonergic or antidopaminergic agents, including antipsychotics, should be discontinued immediately if the above reactions occur and supportive symptomatic treatment should be initiated.

Trazodone hydrochloride tablets should not be used within 14 days of an MAOI [see Warnings and Precautions (5.8) and Drug Interactions (7)].

If concomitant treatment with trazodone hydrochloride tablets and an SSRI, SNRI or a 5-hydroxytryptamine receptor agonist (triptan) is clinically warranted, careful observation of the patient is advised, particularly during treatment initiation and dose increases.

The concomitant use of trazodone hydrochloride tablets with serotonin precursors (such as tryptophan) is not recommended.

5.3 Screening Patients for Bipolar Disorder and Monitoring for Mania/Hypomania

A major depressive episode may be the initial presentation of bipolar disorder. It is generally believed (though not established in controlled trials) that treating such an episode with an antidepressant alone may increase the likelihood of precipitation of a mixed/manic episode in patients at risk for bipolar disorder. Whether any of the symptoms described for clinical worsening and suicide risk represent such a conversion is unknown. However, prior to initiating treatment with an antidepressant, patients with depressive symptoms should be adequately screened to determine if they are at risk for bipolar disorder; such screening should include a detailed psychiatric history, including a family history of suicide, bipolar disorder, and depression. It should be noted that trazodone hydrochloride tablets are not approved for use in treating bipolar depression.

5.4 QT Prolongation and Risk of Sudden Death

Trazodone is known to prolong the QT/QTc interval. Some drugs that prolong the QT/QTc interval can cause torsade de pointes with sudden, unexplained death. The relationship of QT prolongation is clearest for larger increases (20 msec and greater), but it is possible that smaller QT/QTc prolongations may also increase risk, especially in susceptible individuals, such as those with hypokalemia, hypomagnesemia, or a genetic predisposition to prolonged QT/QTc.

Although torsade de pointes has not been observed with the use of trazodone hydrochloride tablets at recommended doses in premarketing trials, experience is too limited to rule out an increased risk. However, there have been postmarketing reports of torsade de pointes with the immediate-release form of trazodone (in the presence of multiple confounding factors), even at doses of 100 mg per day or less.

5.5 Use in Patients With Heart Disease

Trazodone hydrochloride is not recommended for use during the initial recovery phase of myocardial infarction.

Caution should be used when administering trazodone hydrochloride tablets to patients with cardiac disease and such patients should be closely monitored, since antidepressant drugs (including trazodone hydrochloride) may cause cardiac arrhythmias.

QT prolongation has been reported with trazodone therapy [see Warnings and Precautions (5.4)]. Clinical studies in patients with preexisting cardiac disease indicate that trazodone hydrochloride may be arrhythmogenic in some patients in that population. Arrhythmias identified include isolated PVCs, ventricular couplets, tachycardia with syncope, and torsade de pointes. Postmarketing events have been reported at doses of 100 mg or less with the immediate-release form of trazodone.

Concomitant administration of drugs that prolong the QT interval or that are inhibitors of CYP3A4 may increase the risk of cardiac arrhythmia.

5.6 Orthostatic Hypotension and Syncope

Hypotension, including orthostatic hypotension and syncope has been reported in patients receiving trazodone hydrochloride. Concomitant use with an antihypertensive may require a reduction in the dose of the antihypertensive drug.

5.7 Abnormal Bleeding

Postmarketing data have shown an association between use of drugs that interfere with serotonin reuptake and the occurrence of gastrointestinal (GI) bleeding. While no association between trazodone and bleeding events, in particular GI bleeding, was shown, patients should be cautioned about potential risk of bleeding associated with the concomitant use of trazodone and NSAIDs, aspirin, or other drugs that affect coagulation or bleeding. Other bleeding events related to SSRIs and SNRIs have ranged from ecchymosis, hematoma, epistaxis, and petechiae to life-threatening hemorrhages.

5.8 Interaction With MAOIs

In patients receiving serotonergic drugs in combination with a monoamine oxidase inhibitor (MAOI), there have been reports of serious, sometimes fatal reactions including hyperthermia, rigidity, myoclonus, autonomic instability with rapid fluctuation in vital signs, and mental status changes that include extreme agitation progressing to delirium and coma. These reactions have also been reported in patients who have recently discontinued antidepressant treatment and have been started on an MAOI. Some cases presented with features resembling neuroleptic malignant syndrome. Furthermore, limited animal data on the effects of combined use of serotonergic antidepressants and MAOIs suggest that these drugs may act synergistically to elevate blood pressure and evoke behavioral excitation. Therefore, it is recommended that trazodone hydrochloride tablets should not be used in combination with an MAOI or within 14 days of discontinuing treatment with an MAOI. Similarly, at least 14 days should be allowed after stopping trazodone hydrochloride tablets before starting an MAOI.

5.9 Priapism

Rare cases of priapism (painful erections greater than 6 hours in duration) were reported in men receiving trazodone. Priapism, if not treated promptly, can result in irreversible damage to the erectile tissue. Men who have an erection lasting greater than 6 hours, whether painful or not, should immediately discontinue the drug and seek emergency medical attention [see Adverse Reactions (6.2) and Overdosage (10)].

Trazodone should be used with caution in men who have conditions that might predispose them to priapism (e.g., sickle cell anemia, multiple myeloma, or leukemia), or in men with anatomical deformation of the penis (e.g., angulation, cavernosal fibrosis, or Peyronie's disease).

5.10 Hyponatremia

Hyponatremia may occur as a result of treatment with antidepressants. In many cases, this hyponatremia appears to be the result of the syndrome of inappropriate antidiuretic hormone secretion (SIADH). Cases with serum sodium lower than 110 mmol/L have been reported. Elderly patients may be at greater risk of developing hyponatremia with antidepressants. Also, patients taking diuretics or who are otherwise volume-depleted can be at greater risk. Discontinuation of trazodone hydrochloride tablets should be considered in patients with symptomatic hyponatremia and appropriate medical intervention should be instituted.

Signs and symptoms of hyponatremia include headache, difficulty concentrating, memory impairment, confusion, weakness, and unsteadiness, which can lead to falls. Signs and symptoms associated with more severe and/or acute cases have included hallucination, syncope, seizure, coma, respiratory arrest, and death.

5.11 Potential for Cognitive and Motor Impairment

Trazodone hydrochloride tablets may cause somnolence or sedation and may impair the mental and/or physical ability required for the performance of potentially hazardous tasks. Patients should be cautioned about operating hazardous machinery, including automobiles, until they are reasonably certain that the drug treatment does not affect them adversely

5.12 Angle-Closure Glaucoma

Angle-Closure Glaucoma: The pupillary dilation that occurs following use of many antidepressant drugs including trazodone hydrochloride tablets may trigger an angle closure attack in a patient with anatomically narrow angles who does not have a patent iridectomy.

5.13 Discontinuation Symptoms

Withdrawal symptoms including anxiety, agitation and sleep disturbances, have been reported with trazodone. Clinical experience suggests that the dose should be gradually reduced before complete discontinuation of the treatment.

6 ADVERSE REACTIONS

The following serious adverse reactions are described elsewhere in the labeling:

- Clinical Worsening and Suicide Risk [see Boxed Warning and Warnings and Precautions (5.1)]
- Serotonin Syndrome or NMS-Like Reactions [see Warnings and Precautions (5.2)]
- QT Prolongation and Risk of Sudden Death [see Warnings and Precautions (5.4)]
- Orthostatic Hypotension [see Warnings and Precautions (5.6)]
- Abnormal Bleeding Events [see Warnings and Precautions (5.7)]
- Priapism [see Warnings and Precautions (5.9)]
- Hyponatremia [see Warnings and Precautions (5.10)]
- Cognitive and Motor Impairment [see Warnings and Precautions (5.11)]
- Discontinuation Symptoms [see Warnings and Precautions (5.13)]

The most common adverse reactions (reported in ≥ 5% and at twice the rate of placebo) are:

Somnolence/sedation, dizziness, constipation, vision blurred.

Table 2 presents the summary of adverse events (AEs) leading to discontinuation of trazodone hydrochloride tablets treatment with an incidence of at least 1% and at least twice that for placebo.

Table 2: Adverse Reactions With Discontinuation as
Action Taken (≥ 1%) Incidence and Incidence 2x Placebo
 | Trazodone
 | N = 202
Somnolence/Sedation | 8 (4%)
Dizziness | 7 (3.5%)
Confusional state | 2 (1%)
Coordination abnormal | 2 (1%)
Headache | 2 (1%)
Nausea | 2 (1%)
Balance disorder/Gait disturbance | 2 (1%)

6.1 Clinical Studies Experience

The table below is presented solely to indicate the relative frequency of adverse events reported in representative controlled clinical studies conducted to evaluate the safety and efficacy of trazodone hydrochloride.

The figures cited cannot be used to predict concisely the incidence of untoward events in the course of usual medical practice where patient characteristics and other factors often differ from those which prevailed in the clinical trials. These incidence figures, also, cannot be compared with those obtained from other clinical studies involving related drug products and placebo as each group of drug trials is conducted under a different set of conditions.

Table 3: Adverse Reactions: Percentage of Patients (> 2%) as Observed in Controlled Clinical Studies
 | Inpatients |  | Outpatients
 | Trazodone | Placebo | Trazodone | Placebo
Number of Patients | 142 | 95 | 157 | 158
% of Patients Reporting
Allergic
Skin Condition/Edema | 2.8 | 1.1 | 7 | 1.3
Autonomic
Blurred Vision | 6.3 | 4.2 | 14.7 | 3.8
Constipation | 7 | 4.2 | 7.6 | 5.7
Dry Mouth | 14.8 | 8.4 | 33.8 | 20.3
Cardiovascular
Hypertension | 2.1 | 1.1 | 1.3 | *
Hypotension | 7 | 1.1 | 3.8 | 0
Shortness of Breath | * | 1.1 | 1.3 | 0
Syncope | 2.8 | 2.1 | 4.5 | 1.3
Tachycardia/Palpitations | 0 | 0 | 7 | 7
CNS
Anger/Hostility | 3.5 | 6.3 | 1.3 | 2.5
Confusion | 4.9 | 0 | 5.7 | 7.6
Decreased Concentration | 2.8 | 2.1 | 1.3 | 0
Disorientation | 2.1 | 0 | * | 0
Dizziness/Light-Headedness | 19.7 | 5.3 | 28 | 15.2
Drowsiness | 23.9 | 6.3 | 40.8 | 19.6
Excitement | 1.1 | 1.1 | 5.1 | 5.7
Fatigue | 11.3 | 4.2 | 5.7 | 2.5
Headache | 9.9 | 5.3 | 19.8 | 15.8
Insomnia | 9.9 | 10.5 | 6.4 | 12
Impaired Memory | 1.4 | 0 | * | *
Nervousness | 14.8 | 10.5 | 6.4 | 8.2
Gastrointestinal
Abdominal/Gastric Disorder | 3.5 | 4.2 | 5.7 | 4.4
Bad Taste in Mouth | 1.4 | 0 | 0 | 0
Diarrhea | 0 | 1.1 | 4.5 | 1.9
Nausea/Vomiting | 9.9 | 1.1 | 12.7 | 9.5
Musculoskeletal
Musculoskeletal Aches/Pains | 5.6 | 3.2 | 5.1 | 2.5
Neurological
Incoordination | 4.9 | 0 | 1.9 | 0
Paresthesia | 1.4 | 0 | 0 | *
Tremors | 2.8 | 1.1 | 5.1 | 3.8
Sexual Function
Decreased Libido | * | 1.1 | 1.3 | *
Other
Decreased Appetite | 3.5 | 5.3 | 0 | *
Eyes Red/Tired/Itching | 2.8 | 0 | 0 | 0
Head Full-Heavy | 2.8 | 0 | 0 | 0
Malaise | 2.8 | 0 | 0 | 0
Nasal/Sinus Congestion | 2.8 | 0 | 5.7 | 3.2
Nightmares/Vivid Dreams | * | 1.1 | 5.1 | 5.7
Sweating/Clamminess | 1.4 | 1.1 | * | *
Tinnitus | 1.4 | 0 | 0 | *
Weight Gain | 1.4 | 0 | 4.5 | 1.9
Weight Loss | * | 3.2 | 5.7 | 2.5

*Incidence less than 1%

Occasional sinus bradycardia has occurred in long-term studies.

In addition to the relatively common (i.e., greater than 1%) untoward events enumerated above, the following adverse events have been reported to occur in association with the use of trazodone hydrochloride in the controlled clinical studies: akathisia, allergic reaction, anemia, chest pain, delayed urine flow, early menses, flatulence, hallucinations/delusions, hematuria, hyper-salivation, hypomania, impaired speech, impotence, increased appetite, increased libido, increased urinary frequency, missed periods, muscle twitches, numbness, and retrograde ejaculation.

6.2 Postmarketing Experience

Spontaneous reports regarding trazodone hydrochloride received from postmarketing experience include the following: abnormal dreams, agitation, alopecia, anxiety, aphasia, apnea, ataxia, breast enlargement or engorgement, cardiospasm, cerebrovascular accident, chills, cholestasis, clitorism, congestive heart failure, diplopia, edema, extrapyramidal symptoms, grand mal seizures, hallucinations, hemolytic anemia, hirsutism, hyperbilirubinemia, increased amylase, increased salivation, insomnia, leukocytosis, leukonychia, jaundice, lactation, liver enzyme alterations, methemoglobinemia, nausea/vomiting (most frequently), paresthesia, paranoid reaction, priapism [see Warnings and Precautions (5.9) and Patient Counseling Information (17.1)], pruritus, psoriasis, psychosis, rash, stupor, inappropriate ADH syndrome, tardive dyskinesia, unexplained death, urinary incontinence, urinary retention, urticaria, vasodilation, vertigo, and weakness.

Cardiovascular system effects which have been reported include the following: conduction block, orthostatic hypotension and syncope, palpitations, bradycardia, atrial fibrillation, myocardial infarction, cardiac arrest, arrhythmia, ventricular ectopic activity, including ventricular tachycardia and QT prolongation. In postmarketing surveillance, prolonged QT interval, torsade de pointes, and ventricular tachycardia have been reported with the immediate-release form of trazodone at doses of 100 mg per day or less [see Warnings and Precautions (5.4)].

7 DRUG INTERACTIONS

MAOIs

MAOIs should not be used within 14 days of trazodone [see Warnings and Precautions (5.8)].

Central Nervous System (CNS) Depressants

Trazodone may enhance the response to alcohol, barbiturates, and other CNS depressants.

Cytochrome P450 3A4 Inhibitors

In vitro drug metabolism studies suggest that there is a potential for drug interactions when trazodone is given with cytochrome P450 3A4 (CYP3A4) inhibitors. The effect of short-term administration of ritonavir (200 mg twice daily, 4 doses) on the pharmacokinetics of a single dose of trazodone (50 mg) has been studied in 10 healthy subjects. The Cmax of trazodone increased by 34%, the AUC increased 2.4 fold, the half-life increased by 2.2 fold, and the clearance decreased by 52%. Adverse effects including nausea, hypotension, and syncope were observed when ritonavir and trazodone were coadministered. It is likely that ketoconazole, indinavir, and other CYP3A4 inhibitors such as itraconazole may lead to substantial increases in trazodone plasma concentrations with the potential for adverse effects. If trazodone is used with a potent CYP3A4 inhibitor, the risk of cardiac arrhythmia may be increased [see Warnings and Precautions (5.4)] and a lower dose of trazodone should be considered.

Cytochrome P450 Inducers (e.g., Carbamazepine)

Carbamazepine induces CYP3A4. Following coadministration of carbamazepine 400 mg per day with trazodone 100 mg to 300 mg daily, carbamazepine reduced plasma concentrations of trazodone and m-chlorophenlypiperazine (an active metabolite) by 76% and 60% respectively, compared to pre-carbamazepine values. Patients should be closely monitored to see if there is a need for an increased dose of trazodone when taking both drugs.

Digoxin and Phenytoin

Increased serum digoxin or phenytoin levels have been reported in patients receiving trazodone concurrently with either of these drugs. Monitor serum levels and adjust dosages as needed.

Serotonergic Drugs

Based on the mechanism of action of trazodone and the potential for serotonin syndrome, caution is advised when trazodone is coadministered with other drugs that may affect the neurotransmitter systems [see Warnings and Precautions (5.2)].

NSAIDs, Aspirin, or Other Drugs Affecting Coagulation or Bleeding

Due to a possible association between serotonin modulating drugs and gastrointestinal bleeding, patients should be monitored for and cautioned about the potential risk of bleeding associated with the concomitant use of trazodone and NSAIDs, aspirin, or other drugs that affect coagulation or bleeding [see Warnings and Precautions (5.7)].

Warfarin

There have been reports of altered (either increased or decreased) prothrombin times in taking both warfarin and trazodone.

8 USE IN SPECIFIC POPULATIONS

8.1 Pregnancy

Teratogenic Effects

Pregnancy Category C

Trazodone hydrochloride has been shown to cause increased fetal resorption and other adverse effects on the fetus in two studies using the rat when given at dose levels approximately 30 to 50 times the proposed maximum human dose. There was also an increase in congenital anomalies in one of three rabbit studies at approximately 15 to 50 times the maximum human dose. There are no adequate and well-controlled studies in pregnant women. Trazodone hydrochloride should be used during pregnancy only if the potential benefit justifies the potential risk to the fetus.

8.3 Nursing Mothers

Trazodone and/or its metabolites have been found in the milk of lactating rats, suggesting that the drug may be secreted in human milk. Caution should be exercised when trazodone is administered to a nursing woman.

8.4 Pediatric Use

Safety and effectiveness in the pediatric population have not been established [see Boxed Warning and Warnings and Precautions (5.1)]. Trazodone hydrochloride should not be used in children or adolescents.

8.5 Geriatric Use

Reported clinical literature and experience with trazodone has not identified differences in responses between elderly and younger patients. However, as experience in the elderly with trazodone hydrochloride is limited, it should be used with caution in geriatric patients.

Antidepressants have been associated with cases of clinically significant hyponatremia in elderly patients who may be at greater risk for this adverse reaction [see Warnings and Precautions (5.10)].

8.6 Renal Impairment

Trazodone has not been studied in patients with renal impairment. Trazodone should be used with caution in this population.

8.7 Hepatic Impairment

Trazodone has not been studied in patients with hepatic impairment. Trazodone should be used with caution in this population.

9 DRUG ABUSE AND DEPENDENCE

9.1 Controlled Substance

Trazodone hydrochloride tablets are not a controlled substance.

9.2 Abuse

Although trazodone hydrochloride has not been systematically studied in preclinical or clinical studies for its potential for abuse, no indication of drug-seeking behavior was seen in the clinical studies with trazodone hydrochloride. However, it is difficult to predict the extent to which a CNS-active drug will be misused, diverted, and abused. Consequently, physicians should carefully evaluate patients for a history of drug abuse and follow such patients closely, observing them for signs of misuse or abuse of trazodone hydrochloride (e.g., development of tolerance, incrementation of dose, drug-seeking behavior).

10 OVERDOSAGE

10.1 Human Experience

Death from overdose has occurred in patients ingesting trazodone and other CNS depressant drugs concurrently (alcohol; alcohol and chloral hydrate and diazepam; amobarbital; chlordiazepoxide; or meprobamate).

The most severe reactions reported to have occurred with overdose of trazodone alone have been priapism, respiratory arrest, seizures, and ECG changes, including QT prolongation. The reactions reported most frequently have been drowsiness and vomiting. Overdosage may cause an increase in incidence or severity of any of the reported adverse reactions.

10.2 Management of Overdose

There is no specific antidote for trazodone hydrochloride overdose.

Treatment should consist of those general measures employed in the management of overdosage with any drug effective in the treatment of major depressive disorder.

Ensure an adequate airway, oxygenation and ventilation. Monitor cardiac rhythm and vital signs.

General supportive and symptomatic measures are also recommended. Induction of emesis is not recommended. Gastric lavage with a large bore orogastric tube with appropriate airway protection, if needed, may be indicated if performed soon after ingestion, or in symptomatic patients. Activated charcoal should be administered. Forced diuresis may be useful in facilitating elimination of the drug.

In managing overdosage, consider the possibility of multiple drug involvement. The physician should consider contacting a poison control center for additional information on the treatment of any overdose.

11 DESCRIPTION

Trazodone hydrochloride, USP is an antidepressant chemically unrelated to tricyclic, tetracyclic, or other known antidepressant agents. Trazodone hydrochloride, USP is a triazolopyridine derivative designated as 2-[3-[4-(3-chlorophenyl)-1-piperazinyl]propyl]-1,2,4-triazolo[4, 3-a]pyridin-3(2H)-one hydrochloride. It is a white, odorless crystalline powder which is freely soluble in water. The structural formula is represented as follows:

Each tablet, for oral administration, contains 50 mg, 100 mg or 150 mg of trazodone hydrochloride, USP. In addition, each tablet contains colloidal silicon dioxide, lactose anhydrous, magnesium stearate, microcrystalline cellulose and sodium starch glycolate.

12 CLINICAL PHARMACOLOGY

12.1 Mechanism of Action

The mechanism of trazodone’s antidepressant action is not fully understood, but is thought to be related to its potentiation of serotonergic activity in the CNS.

12.2 Pharmacodynamics

Preclinical studies have shown that trazodone selectively inhibits neuronal reuptake of serotonin and acts as an antagonist at 5-HT-2A/2C serotonin receptors.

Trazodone is not a monoamine oxidase inhibitor and, unlike amphetamine-type drugs, does not stimulate the central nervous system.

Trazodone antagonizes alpha 1-adrenergic receptors, a property which may be associated with postural hypotension.

12.3 Pharmacokinetics

Absorption

In humans, trazodone hydrochloride is well absorbed after oral administration without selective localization in any tissue. When trazodone hydrochloride is taken shortly after ingestion of food, there may be an increase in the amount of drug absorbed, a decrease in maximum concentration and a lengthening in the time to maximum concentration. Peak plasma levels occur approximately one hour after dosing when trazodone hydrochloride is taken on an empty stomach or 2 hours after dosing when taken with food.

Metabolism

In vitro studies in human liver microsomes show that trazodone is metabolized, via oxidative cleavage, to an active metabolite, m-chlorophenylpiperazine (mCPP) by CYP3A4. Other metabolic pathways that may be involved in the metabolism of trazodone have not been well characterized. Trazodone is extensively metabolized; less than 1% of an oral dose is excreted unchanged in the urine.

Elimination

In some patients trazodone may accumulate in the plasma.

Protein Binding

Trazodone is 89 to 95% protein bound in vitro at concentrations attained with therapeutic doses in humans.

13 NONCLINICAL TOXICOLOGY

13.1 Carcinogenesis, Mutagenesis, Impairment of Fertility

No drug- or dose-related occurrence of carcinogenesis was evident in rats receiving trazodone in daily oral doses up to 300 mg/kg for 18 months.

14 CLINICAL STUDIES

The efficacy and safety of trazodone hydrochloride was established from both inpatient and outpatient trials of the trazodone immediate release formulation in the treatment of major depressive disorder.

16 HOW SUPPLIED/STORAGE AND HANDLING

Product: 53002-1105

NDC: 53002-1105-3 30 TABLET in a BOTTLE

NDC: 53002-1105-6 60 TABLET in a BOTTLE

NDC: 53002-1105-0 100 TABLET in a BOTTLE

Product: 53002-1132

NDC: 53002-1132-1 10 TABLET in a BOTTLE

NDC: 53002-1132-3 30 TABLET in a BOTTLE

NDC: 53002-1132-6 60 TABLET in a BOTTLE

NDC: 53002-1132-0 100 TABLET in a BOTTLE

17 PATIENT COUNSELING INFORMATION

See FDA-approved Medication Guide

17.1 Information for Patients

Prescribers or other health professionals should inform patients, their families, and their caregivers about the benefits and risks associated with treatment with trazodone hydrochloride and should counsel them in its appropriate use.

Patients should be warned that:

- There is a potential for increased risk of suicidal thoughts especially in children, teenagers and young adults.
- The following symptoms should be reported to the physician: anxiety, agitation, panic attacks, insomnia, irritability, hostility, aggressiveness, impulsivity, akathisia, hypomania and mania.
- They should inform their physician if they have a history of bipolar disorder, cardiac disease or myocardial infarction.
- Serotonin syndrome could occur and symptoms may include changes in mental status (e.g., agitation, hallucinations, and coma), autonomic instability (e.g., tachycardia, labile blood pressure, and hyperthermia), neuromuscular aberrations (e.g., hyperreflexia, incoordination) and/or gastrointestinal symptoms (e.g., nausea, vomiting, and diarrhea).
- Trazodone hydrochloride has been associated with the occurrence of priapism.
- There is a potential for hypotension, including orthostatic hypotension and syncope.
- There is a potential risk of bleeding (including life-threatening hemorrhages) and bleeding related events (including ecchymosis, hematoma, epistaxis, and petechiae) with the concomitant use of trazodone hydrochloride and NSAIDs, aspirin, or other drugs that affect coagulation or bleeding.
- Withdrawal symptoms including anxiety, agitation and sleep disturbances, have been reported with trazodone. Clinical experience suggests that the dose should be gradually reduced.
- Patients should be advised that taking trazodone hydrochloride tablets can cause mild pupillary dilation, which in susceptible individuals, can lead to an episode of angle-closure glaucoma. Pre-existing glaucoma is almost always open-angle glaucoma because angle closure glaucoma, when diagnosed, can be treated definitively with iridectomy. Open-angle glaucoma is not a risk factor for angle-closure glaucoma. Patients may wish to be examined to determine whether they are susceptible to angle closure, and have a prophylactic procedure (e.g., iridectomy), if they are susceptible. [see Warnings and Precautions (5.12)]

Patients should be counseled that:

- Trazodone may cause somnolence or sedation and may impair the mental and/or physical ability required for the performance of potentially hazardous tasks. Patients should be cautioned about operating hazardous machinery, including automobiles until they are reasonably certain that the drug treatment does not affect them.
- Trazodone may enhance the response to alcohol, barbiturates, and other CNS depressants.
- Women who intend to become pregnant or who are breastfeeding should discuss with a physician whether they should continue to use trazodone, since use in pregnant and nursing women is not recommended.

Important Administration Instructions:

- Trazodone hydrochloride tablets should be swallowed whole or broken in half along the score line.
- Trazodone hydrochloride tablets should be taken shortly after a meal or light snack.

Manufactured In Croatia By:

PLIVA HRVATSKA d.o.o.

Zagreb, Croatia

Manufactured For:

TEVA PHARMACEUTICALS USA, INC.

North Wales, PA 19454

Rev. F 3/2016

MEDICATION GUIDE

Trazodone Hydrochloride (traz' oh done hye'' droe klor' ide) Tablets USP

Read the Medication Guide that comes with trazodone hydrochloride tablets before you start taking it and each time you get a refill. There may be new information. This information does not take the place of talking to your healthcare provider about your medical condition or treatment. Talk to your healthcare provider or pharmacist if there is something you do not understand or you want to learn about trazodone hydrochloride tablets.

What is the most important information I should know about trazodone hydrochloride tablets?

Antidepressant medicines, depression or other serious mental illnesses, and suicidal thoughts or actions: Talk to your healthcare provider about:

- All risks and benefits of treatment with antidepressant medicines
- All treatment choices for depression or other serious mental illnesses
1. Antidepressant medicines may increase suicidal thoughts or actions in some children, teenagers, and young adults within the first few months of treatment.
2. Depression and other serious mental illnesses are the most important causes of suicidal thoughts and actions. Some people may have a higher risk of having suicidal thoughts or actions. These include people who have or have a family history of bipolar illness (also called manic-depressive illness) or suicidal thoughts or actions.
3. How can I watch for and try to prevent suicidal thoughts and actions?
- Pay close attention to any changes, especially sudden changes in mood, behaviors, thoughts, or feelings. This is very important when an antidepressant medicine is started or when the dose is changed.
- Call your healthcare provider right away to report new or sudden changes in mood, behavior, thoughts or feelings.
- Keep all follow-up visits with your healthcare provider as scheduled. Call your healthcare provider between visits as needed, especially if you are worried about symptoms.
Call a healthcare provider right away if you have any of the following symptoms, especially if they are new, worse, or worry you:
- Thoughts about suicide or dying
- Attempts to commit suicide
- New or worse depression
- New or worse anxiety
- Feeling very agitated or restless
- Panic attacks
- Trouble sleeping (insomnia)
- New or worse irritability
- Acting aggressive, being angry or violent
- Acting on dangerous impulses
- An extreme increase in activity and talking (mania)
- Other unusual changes in behavior or mood
4. Visual problems:
- eye pain
- changes in vision
- swelling or redness in or around the eye

Only some people are at risk for these problems. You may want to undergo an eye examination to see if you are at risk and receive preventative treatment if you are.

What else do I need to know about antidepressant medicines?

Never stop an antidepressant medicine without first talking to a healthcare provider. Stopping an antidepressant medicine suddenly can cause other symptoms.

Antidepressants are medicines used to treat depression and other illnesses. It is important to discuss all the risks of treating depression and also the risks of not treating it. You should discuss all treatment choices with your healthcare provider, not just the use of antidepressants.

Antidepressant medicines have other side effects. Talk to your healthcare provider about the side effects of your medicines.

Antidepressant medicines can interact with other medicines. Know all of the medicines that you take. Keep a list of all medicines to show your healthcare provider. Do not start new medicines without first checking with your healthcare provider.

5. Trazodone hydrochloride tablets are not approved for use in children. Talk to your healthcare provider for more information.

What are trazodone hydrochloride tablets?

Trazodone hydrochloride tablets are a prescription medicine used to treat major depressive disorder in adults.

What should I tell my healthcare provider before taking trazodone hydrochloride tablets?

Before you take trazodone hydrochloride tablets tell your healthcare provider if you:

- have heart problems, including QT prolongation or a family history of it
- have ever had a heart attack
- have bipolar disorder
- have liver or kidney problems
- have other serious medical conditions
- are pregnant or plan to become pregnant. Trazodone hydrochloride tablets may harm your unborn baby. Talk to your healthcare provider if you are pregnant or plan to become pregnant.
- are breastfeeding or plan to breastfeed. It is not known if trazodone hydrochloride passes into your breast milk. You and your healthcare provider should decide if you will take trazodone hydrochloride or breastfeed.
- have taken a Monoamine Oxidase Inhibitor (MAOI) or if you have stopped taking an MAOI in the last 2 weeks.

Tell your healthcare provider about all the medicines you take, including prescription and non-prescription medicines, vitamins, and herbal supplements.

Using trazodone hydrochloride tablets with certain other medicines can affect each other causing serious side effects.

Know the medicines you take. Keep a list of them and show it to your healthcare provider and pharmacist when you get a new medicine.

How should I take trazodone hydrochloride tablets?

- Take trazodone hydrochloride tablets exactly as your healthcare provider tells you.
- Trazodone hydrochloride tablets should be taken shortly after a meal or light snack.
- If you feel drowsy after taking trazodone hydrochloride tablets, talk to your healthcare provider. Your healthcare provider may change your dose or the time of day you take your trazodone hydrochloride tablets.
- Do not stop taking trazodone hydrochloride tablets without talking to your healthcare provider.
- Trazodone hydrochloride tablets should be swallowed whole or broken in half along the score line. Do not chew or crush trazodone hydrochloride tablets. Tell your healthcare provider if you cannot swallow trazodone either whole or as a half tablet.
- If you take too much trazodone hydrochloride, call your doctor or go to the nearest emergency room right away.

What should I avoid while taking trazodone hydrochloride tablets?

- Do not drive, operate heavy machinery, or do other dangerous activities until you know how trazodone hydrochloride tablets affect you. Trazodone hydrochloride tablets can slow your thinking and motor skills.
- Do not drink alcohol or take other medicines that make you sleepy or dizzy while taking trazodone hydrochloride tablets until you talk with your healthcare provider. Trazodone hydrochloride tablets may make your sleepiness or dizziness worse if you take it with alcohol or other medicines that cause sleepiness or dizziness.

What are the possible side effects of trazodone hydrochloride tablets?

Trazodone hydrochloride tablets can cause serious side effects or death. See “What is the most important information I should know about trazodone hydrochloride tablets?”

Serious side effects include:

- Serotonin syndrome. Symptoms of serotonin syndrome include: agitation, hallucinations, problems with coordination, fast heartbeat, tight muscles, trouble walking, nausea, vomiting, diarrhea.
- Feeling high or in a very good mood, then becoming irritable, or having too much energy, feeling like you have to keep talking or do not sleep (mania).
- Irregular or fast heartbeat or faint (QT prolongation).
- Low blood pressure. You feel dizzy or faint when you change positions (go from sitting to standing).
- Unusual bruising or bleeding.
- Erection lasting for more than 6 hours (priapism).
- Low sodium in your blood (hyponatremia). Symptoms of hyponatremia include: headache, feeling weak, feeling confused, trouble concentrating, memory problems and feeling unsteady when you walk.
- Withdrawal symptoms. Symptoms of withdrawal can include anxiety, agitation, and sleep problems. Do not stop taking trazodone hydrochloride tablets without talking to your healthcare provider.

Get medical help right away, if you have any of the symptoms listed above.

The most common side effects of trazodone hydrochloride tablets include:

- Sleepiness
- Dizziness
- Constipation
- Blurry vision

Tell your healthcare provider if you have any side effect that bothers you or that does not go away.

These are not all the possible side effects of trazodone hydrochloride tablets. For more information, ask your healthcare provider or pharmacist.

Call your doctor for medical advice about side effects. You may report side effects to FDA at 1-800-FDA-1088.

How should I store trazodone hydrochloride tablets?

- Store trazodone hydrochloride tablets between 20° to 25°C (68° to 77°F).
- Keep in tight container
- Keep out of the light
- Safely throw away medicine that is out of date or no longer needed.

Keep trazodone hydrochloride tablets and all medicines out of the reach of children.

General information about the safe and effective use of trazodone hydrochloride tablets.

Medicines are sometimes prescribed for purposes other than those listed in a Medication Guide. Do not use trazodone hydrochloride tablets for a condition for which it was not prescribed. Do not give trazodone hydrochloride tablets to other people, even if they have the same symptoms that you have. It may harm them.

This Medication Guide summarizes the most important information about trazodone hydrochloride tablets. If you would like more information, talk with your healthcare provider. You can ask your pharmacist or healthcare provider for information about trazodone hydrochloride tablets that is written for health professionals.

For more information, call 1-888-838-2872.

What are the ingredients in trazodone hydrochloride tablets?

Active ingredient: trazodone hydrochloride

Inactive ingredients: colloidal silicon dioxide, lactose anhydrous, magnesium stearate, microcrystalline cellulose and sodium starch glycolate.

This Medication Guide has been approved by the U.S. Food and Drug Administration.

Manufactured In Croatia By:

PLIVA HRVATSKA d.o.o.

Zagreb, Croatia

Manufactured For:

TEVA PHARMACEUTICALS USA, INC.

North Wales, PA 19454

Rev. C 3/2016